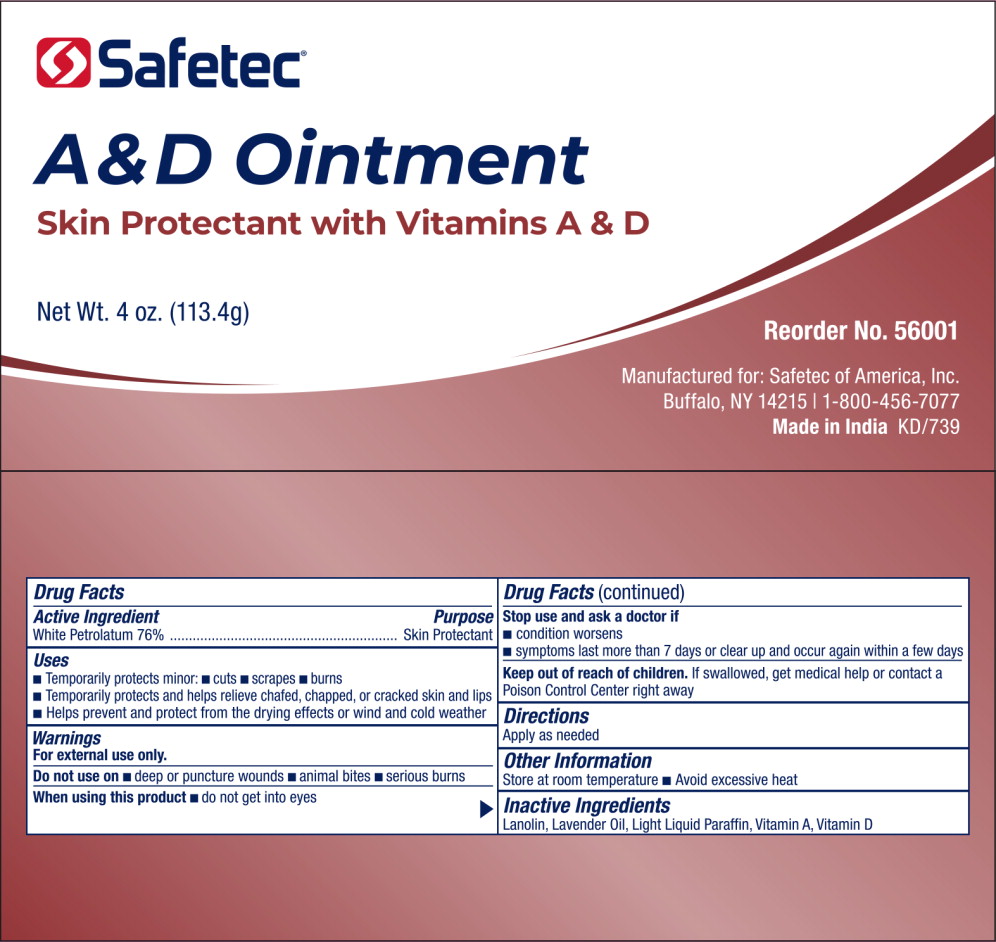 DRUG LABEL: A and D
NDC: 61010-4405 | Form: OINTMENT
Manufacturer: Safetec of America, Inc.
Category: otc | Type: HUMAN OTC DRUG LABEL
Date: 20240209

ACTIVE INGREDIENTS: PETROLATUM 76 g/100 g
INACTIVE INGREDIENTS: LANOLIN; LAVENDER OIL; LIGHT MINERAL OIL; VITAMIN A ACETATE; CHOLECALCIFEROL

61010-4405, A and D Ointment

Drug Facts

Active Ingredient

White Petrolatum 76 %

Purpose

Skin Protectant

Use

- Temporarily protects minor:
  - cuts
  - scrapes
  - burns
- Temporarily protects and helps relieve chafed, chapped, or cracked skin and lips
- Helps prevent and protect from the drying effects or wind and cold weather

Warnings

For external use only.

Do not use on

- deep or puncture wounds
- animal bites
- serious burns

When using this product:

- do not get into eyes

Stop use and ask a doctor if:

- condition worsens
- symptoms last more than 7 days or clear up and occur again within a few days.

Keep out of reach of children. If swallowed, get medical help or contact a Poison Control Center right away

Directions

Apply as needed

Other Information

Store at room temperature

- Avoid excessive heat

Inactive Ingredients

Lanolin, Lavender Oil, Light Liquid Paraffin, Vitamin A, Vitamin D

Principal Display Panel –Tube Label

Safetec®

A&D Ointment

Skin Protectant with Vitamins A & D

Net Wt. 4oz. (113.4g)

Reorder No. 56001

Manufactured for: Safetec of America INC.

Buffalo, NY 14215 | 1-800-456-7077

Made in IndiaKD/739